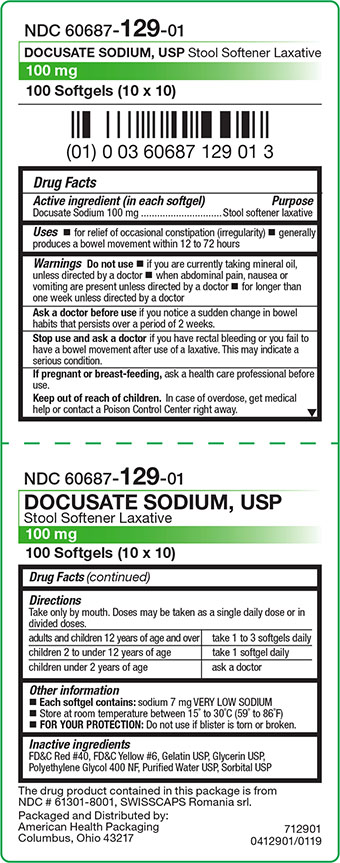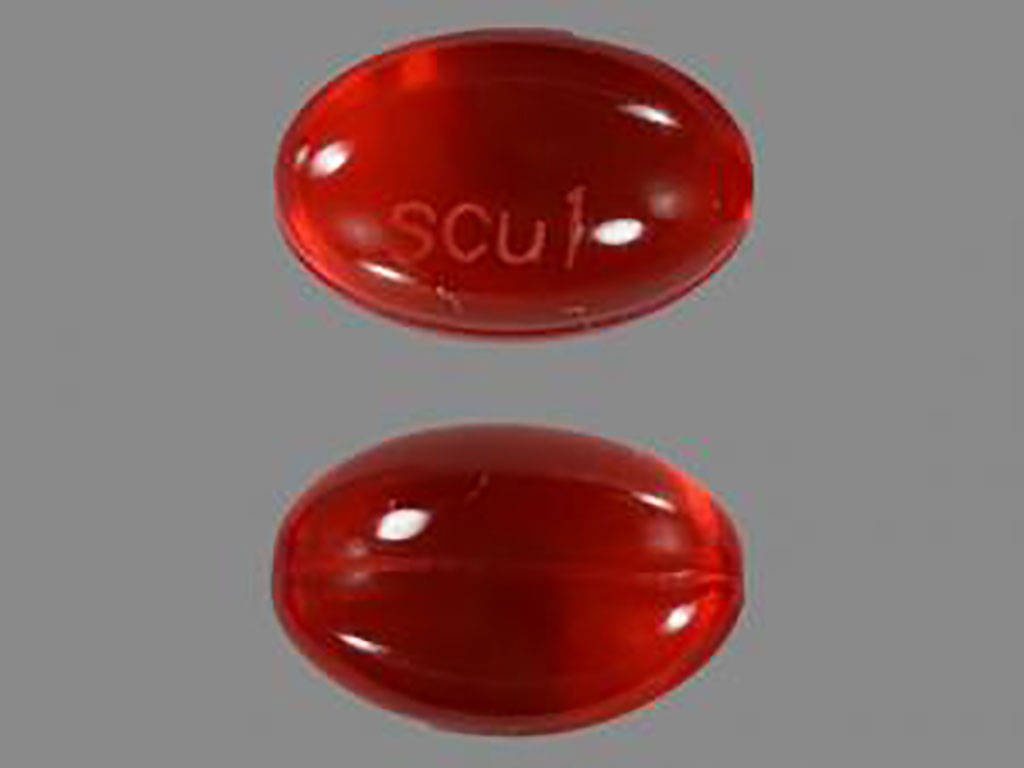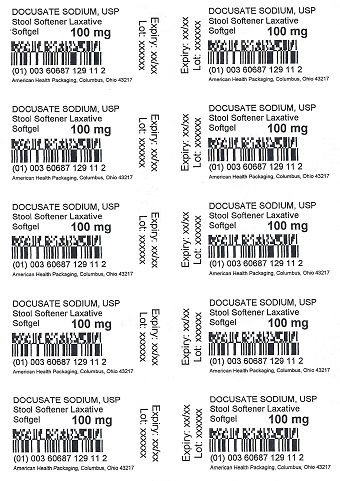 DRUG LABEL: Docusate Sodium
NDC: 60687-129 | Form: CAPSULE, LIQUID FILLED
Manufacturer: American Health Packaging
Category: otc | Type: HUMAN OTC DRUG LABEL
Date: 20241121

ACTIVE INGREDIENTS: DOCUSATE SODIUM 100 mg/1 1
INACTIVE INGREDIENTS: FD&C RED NO. 40; FD&C YELLOW NO. 6; GELATIN, UNSPECIFIED; GLYCERIN; POLYETHYLENE GLYCOL 400; WATER; SORBITOL

DOCUSATE SODIUM, USP
Stool Softener Laxative
Drug Facts

Active ingredient (in each softgel)

Docusate Sodium 100 mg

Purpose

Stool softener laxative

Uses

- for relief of occasional constipation (irregularity)
- generally produces a bowel movement within 12 to 72 hours

Warnings

Do not use

- if you are currently taking mineral oil, unless directed by a doctor
- when abdominal pain, nausea or vomiting are present unless directed by a doctor
- for longer than one week unless directed by a doctor

Ask a doctor before use if you notice a sudden change in bowel habits that persists over a period of 2 weeks.

Stop use and ask a doctor if you have rectal bleeding or you fail to have a bowel movement after use of a laxative. This may indicate a serious condition.

If pregnant or breast-feeding, ask a health care professional before use.

Keep out of reach of children. In case of overdose, get medical help or contact a Poison Control Center right away.

Directions

Take only by mouth. Doses may be taken as a single daily dose or in divided doses.

adults and children 12 years of age and over | take 1 to 3 softgels daily
children 2 to under 12 years of age | take 1 softgel daily
children under 2 years of age | ask a doctor

Other information

- Each softgel contains: sodium 7 mg VERY LOW SODIUM
- Store at room temperature between 15° to 30°C (59° to 86°F)
- FOR YOUR PROTECTION: Do not use if blister is torn or broken.

Inactive ingredients

FD&C Red #40, FD&C Yellow #6, Gelatin USP, Glycerin USP, Polyethylene Glycol 400 NF, Purified Water USP, Sorbital USP

The drug product contained in this package is from NDC # 61301-8001, SWISSCAPS Romania srl.

Distributed by:
American Health Packaging
2550 John Glenn Avenue, Suite A
Columbus, OH 43217

712901
0412901/0216PS

Principal Display Panel – Carton – 100 mg

NDC 60687- 129-01

DOCUSATE SODIUM, USP
Stool Softener Laxative

100 mg

100 Softgels (10 x 10)

The drug product contained in this package is from
NDC # 61301-8001, SWISSCAPS Romania srl.

Packaged and Distributed by:
American Health Packaging
Columbus, OH 43217

712901
0412901/0119

Principal Display Panel - Blister – 100 mg

DOCUSATE SODIUM, USP
Stool Softener Laxative
Softgel 100 mg